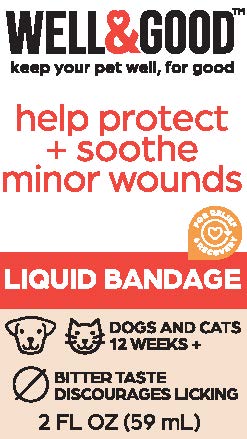 DRUG LABEL: Well and Good Liquid Bandage
NDC: 77720-029 | Form: SPRAY
Manufacturer: Skaffles Group Limited Liability Company
Category: animal | Type: OTC ANIMAL DRUG LABEL
Date: 20220915

ACTIVE INGREDIENTS: ALLANTOIN 4 g/100 mL
INACTIVE INGREDIENTS: WATER; POLYESTER-5 (TG-38); DMDM HYDANTOIN; IODOPROPYNYL BUTYLCARBAMATE; PROPYLENE GLYCOL; METHYLPARABEN; PROPYLPARABEN; DIAZOLIDINYL UREA; ALOE VERA LEAF; GLYCERIN

Liquid Bandage

WARNINGS AND PRECAUTIONS

DIRECTIONS: Thoroughly
clean and dry affected
area. Lightly spray the
wound and let dry.

INDICATIONS AND USAGE

DIRECTIONS: Thoroughly
clean and dry affected
area. Lightly spray the
wound and let dry.

For use on animals
12 weeks or older.

INGREDIENTS
Water, Polyester-5,
Allantoin, DMDM Hydantoin,
lodopropynyl
Butylcarbamate, Propylene
Glycol, Methylparaben,
Propylparaben, Diazolidinyl
Urea, Aloe Barbadensis,
Glycerin.

Principal Display Panel

WELL&GOOD™
keep your pet well, for good

help protect + sooth minor wounds

For Relief & Recovery

LIQUID BANDAGE FOR DOGS AND CATS 12 WEEKS+

BITTER TASTE DISCOURAGES LICKING

2 FL OZ (59 ml)

Distributed by: International Pet Supplies and Distribution, Inc., San Diego, CA 92127

Contact us at 1.855.FAQ.Petco

©2022 Petco Animal Supplies, Inc.

All Rights Reserved. Made in China